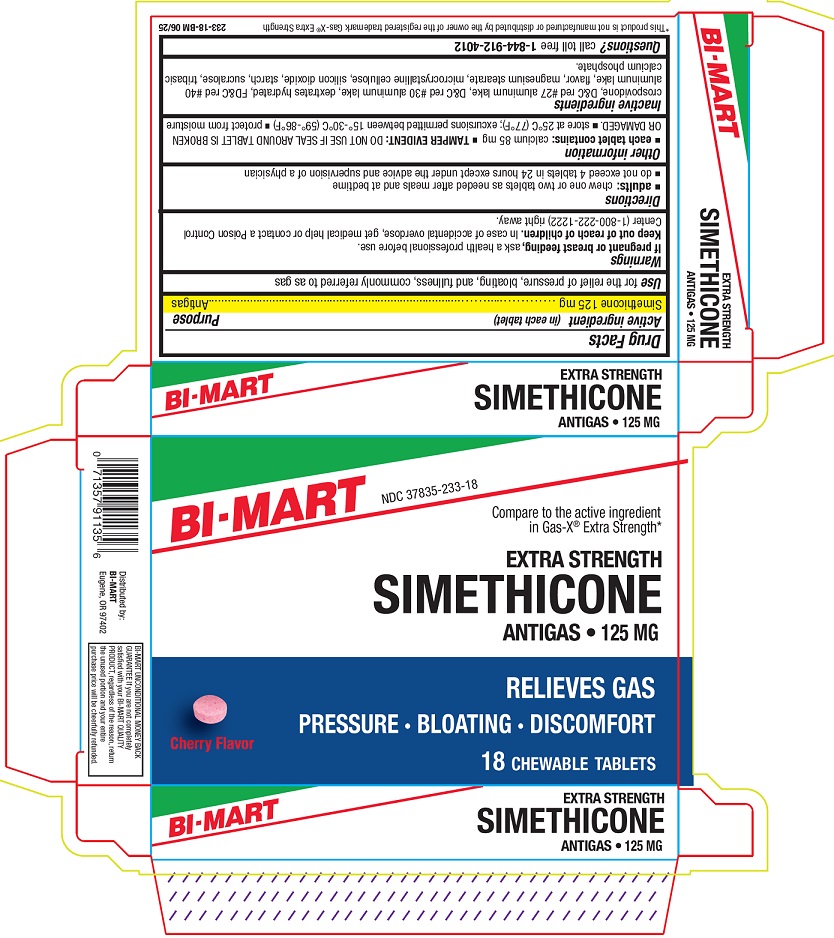 DRUG LABEL: EXTRA STRENGTH SIMETHICONE
NDC: 37835-233 | Form: TABLET, CHEWABLE
Manufacturer: Bi-Mart
Category: otc | Type: HUMAN OTC DRUG LABEL
Date: 20250901

ACTIVE INGREDIENTS: DIMETHICONE 125 mg/1 1
INACTIVE INGREDIENTS: CROSPOVIDONE; D&C RED NO. 27 ALUMINUM LAKE; D&C RED NO. 30 ALUMINUM LAKE; DEXTROSE MONOHYDRATE; FD&C RED NO. 40 ALUMINUM LAKE; MAGNESIUM STEARATE; MICROCRYSTALLINE CELLULOSE; SILICON DIOXIDE; STARCH, CORN; SUCRALOSE; TRIBASIC CALCIUM PHOSPHATE

Active ingredient (in each tablet)

Simethicone 125 mg

Purpose

Antigas

Uses

for the relief of pressure, bloating, and fullness commonly referred to as gas

If pregnant or breast feeding,

ask a health professional before use.

Keep out of reach of children.

In case of accidental overdose, get medical help or a Poison Control Center (1-800-222-1222) right away.

Directions

- adults:chew one or two tablets as needed after meals and at bedtime
- do not exceed 4 tablets in 24 hours except under the advice and supervision of a physician

Other information

- each tablet contains:calcium 85 mg
- TAMPER EVIDENT:DO NOT USE IF SEAL AROUN TABLET IS BROKEN OR DAMAGED
- store at 25°C (77°F); excursions permitted between 15°-30°C (59°-86°F)
- protect from moisture

Inactive ingredients

crospovidone, D&C red #27 aluminum lake, D&C red #30 aluminum lake, dextrates hydrated, FD&C red #40 aluminum lake, flavor, magnesium stearate, microcrystalline cellulose, silicon dioxide, starch, sucralose, tribasic calcium phosphate.

Questions?

call toll free 1-844-912-4012